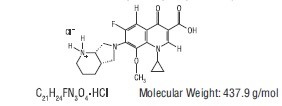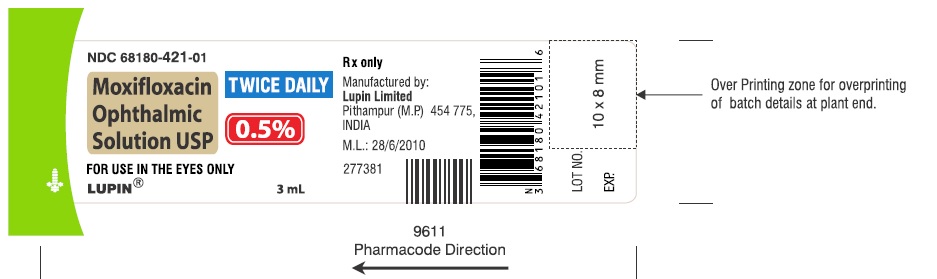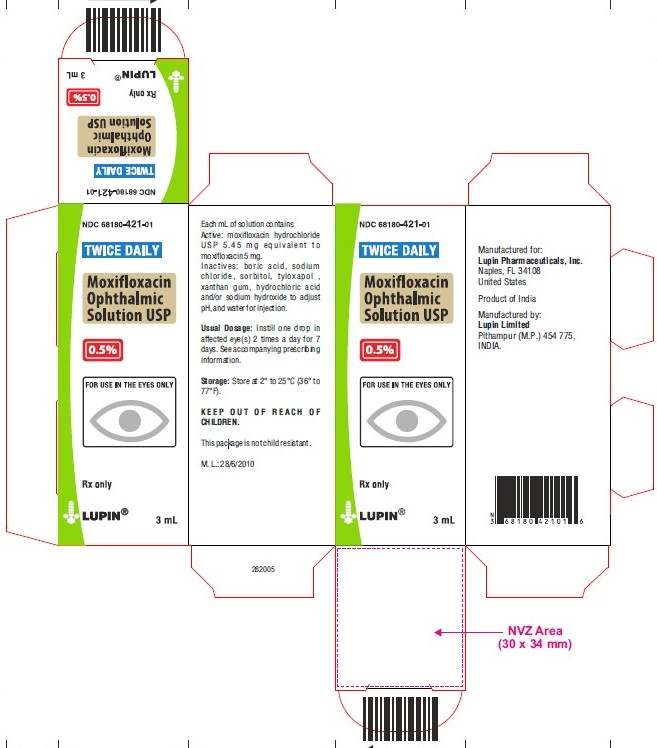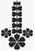 DRUG LABEL: MOXIFLOXACIN
NDC: 68180-421 | Form: SOLUTION
Manufacturer: Lupin Pharmaceuticals, Inc.
Category: prescription | Type: HUMAN PRESCRIPTION DRUG LABEL
Date: 20251013

ACTIVE INGREDIENTS: MOXIFLOXACIN HYDROCHLORIDE 5 mg/1 mL

HIGHLIGHTS OF PRESCRIBING INFORMATION

These highlights do not include all the information needed to use Moxifloxacin Ophthalmic Solution USP, 0.5% safely and effectively. See full prescribing information for Moxifloxacin Ophthalmic Solution USP, 0.5%.
MOXIFLOXACIN Ophthalmic Solution USP, 0.5%
for topical ophthalmic use
Initial U.S. Approval: 1999

RECENT MAJOR CHANGES

Warnings and Precautions (5.1) 8/2021

1 INDICATIONS AND USAGE

Moxifloxacin Ophthalmic Solution USP is a topical fluoroquinolone anti-infective indicated for the treatment of bacterial conjunctivitis caused by susceptible strains of the following organisms:

Aerococcus viridans*, Corynebacterium macginleyi*, Enterococcus faecalis*, Micrococcus luteus*, Staphylococcus arlettae*, Staphylococcus aureus, Staphylococcus capitis, Staphylococcus epidermidis, Staphylococcus haemolyticus, Staphylococcus hominis, Staphylococcus saprophyticus*, Staphylococcus warneri*, Streptococcus mitis*, Streptococcus pneumoniae, Streptococcus parasanguinis*, Escherichia coli*, Haemophilus influenzae, Klebsiella pneumoniae*, Propionibacterium acnes, Chlamydia trachomatis*

*Efficacy for this organism was studied in fewer than 10 infections. (1)

2 DOSAGE AND ADMINISTRATION

Instill 1 drop in the affected eye(s) 2 times daily for 7 days. (2)

3 DOSAGE FORMS AND STRENGTHS

Ophthalmic solution containing moxifloxacin 0.5%. (3)

4 CONTRAINDICATIONS

None. (4)

5 WARNINGS AND PRECAUTIONS

- Corneal Endothelial Damage and Toxic Anterior Segment Syndrome : Intracameral injections will cause harm to endothelium. (5.1)
- Hypersensitivity Reactions : Hypersensitivity and anaphylaxis have been reported with systemic use of moxifloxacin. (5.2)
- Prolonged Use : May result in overgrowth of non-susceptible organisms, including fungi. If superinfection occurs, discontinue use and institute alternative therapy. (5.3)
- Avoid Contact Lens Wear : Patients should not wear contact lenses if they have signs or symptoms of bacterial conjunctivitis. (5.4)

6 ADVERSE REACTIONS

The most common adverse reactions reported in 1% to 2% of patients were eye irritation, pyrexia, and conjunctivitis. (6)

To report SUSPECTED ADVERSE REACTIONS, contact Lupin Pharmaceuticals, Inc. at 1-800-399-2561 or FDA at 1-800-FDA-1088 or www.fda.gov/medwatch.

FULL PRESCRIBING INFORMATION

1 INDICATIONS AND USAGE

Moxifloxacin ophthalmic solution USP is indicated for the treatment of bacterial conjunctivitis caused by susceptible strains of the following organisms:

Aerococcus viridans*

Corynebacterium macginleyi*

Enterococcus faecalis*

Micrococcus luteus*

Staphylococcus arlettae*

Staphylococcus aureus

Staphylococcus capitis

Staphylococcus epidermidis

Staphylococcus haemolyticus

Staphylococcus hominis

Staphylococcus saprophyticus*

Staphylococcus warneri*

Streptococcus mitis*

Streptococcus pneumoniae

Streptococcus parasanguinis*

Escherichia coli*

Haemophilus influenza

Klebsiella pneumoniae*

Propionibacterium acnes

Chlamydia trachomatis*

*Efficacy for this organism was studied in fewer than 10 infections.

2 DOSAGE AND ADMINISTRATION

Instill 1 drop in the affected eye(s) 2 times daily for 7 days.

3 DOSAGE FORMS AND STRENGTHS

Ophthalmic solution containing moxifloxacin 0.5%.

4 CONTRAINDICATIONS

None.

5 WARNINGS AND PRECAUTIONS

5.1 Corneal Endothelial Damage and Toxic Anterior Segment Syndrome

NOT FOR INTRACAMERAL USE OR INJECTION. Moxifloxacin ophthalmic solution will cause damage to the corneal endothelium if introduced directly into the anterior chamber of the eye.

Toxic Anterior Segment Syndrome (TASS) has been reported following intraocular administration of moxifloxacin. TASS is typically characterized by anterior chamber inflammatory reactions, such as fibrin, cell or flare and corneal edema, but other events, such as hypopyon, keratic precipitates or vitreous opacities may also occur.

5.2 Hypersensitivity Reactions

In patients receiving systemically administered quinolones, including moxifloxacin, serious and occasionally fatal hypersensitivity (anaphylactic) reactions have been reported, some following the first dose. Some reactions were accompanied by cardiovascular collapse, loss of consciousness, angioedema (including laryngeal, pharyngeal or facial edema), airway obstruction, dyspnea, urticaria, and itching. If an allergic reaction to moxifloxacin occurs, discontinue use of the drug. Serious acute hypersensitivity reactions may require immediate emergency treatment. Oxygen and airway management should be administered as clinically indicated.

5.3 Growth of Resistant Organisms With Prolonged Use

As with other anti-infectives, prolonged use may result in overgrowth of non-susceptible organisms, including fungi. If superinfection occurs, discontinue use and institute alternative therapy. Whenever clinical judgment dictates, the patient should be examined with the aid of magnification, such as slit-lamp biomicroscopy, and, where appropriate, fluorescein staining.

5.4 Avoidance of Contact Lens Wear

Patients should be advised not to wear contact lenses if they have signs or symptoms of bacterial conjunctivitis.

6 ADVERSE REACTIONS

Because clinical trials are conducted under widely varying conditions, adverse reaction rates observed in the clinical trials of a drug cannot be directly compared to the rates in the clinical trials of another drug and may not reflect the rates observed in practice.

The data described below reflect exposure to moxifloxacin ophthalmic solution in 1263 patients, between 4 months and 92 years of age, with signs and symptoms of bacterial conjunctivitis. The most frequently reported adverse reactions were eye irritation, pyrexia and conjunctivitis, reported in 1% to 2% of patients.

8 USE IN SPECIFIC POPULATIONS

8.1 Pregnancy

Risk Summary

There are no adequate and well-controlled studies with moxifloxacin ophthalmic solution in pregnant women to inform any drug-associated risks.

Oral administration of moxifloxacin to pregnant rats and monkeys and intravenously to pregnant rabbits during the period of organogenesis did not produce adverse maternal or fetal effects at clinically relevant doses. Oral administration of moxifloxacin to pregnant rats during late gestation through lactation did not produce adverse maternal, fetal or neonatal effects at clinically relevant doses (see Data).

Data

Animal Data

Embryo-fetal studies were conducted in pregnant rats administered with 20, 100, or 500 mg/kg/day moxifloxacin by oral gavage on Gestation Days 6 to 17, to target the period of organogenesis. Decreased fetal body weight and delayed skeletal development were observed at 500 mg/kg/day (1420 times the human area under the curve (AUC) at the recommended human ophthalmic dose). The No-Observed-Adverse-Effect-Level (NOAEL) for developmental toxicity was 100 mg/kg/day (152 times the human AUC at the recommended human ophthalmic dose).

Embryo-fetal studies were conducted in pregnant rabbits administered with 2, 6.5, or 20 mg/kg/day moxifloxacin by intravenous administration on Gestation Days 6 to 20, to target the period of organogenesis. Abortions, increased incidence of fetal malformations, delayed fetal skeletal ossification, and reduced placental and fetal body weights were observed at 20 mg/kg/day (5569 times the human AUC at the recommended human ophthalmic dose), a dose that produced maternal body weight loss and death. The NOAEL for developmental toxicity was 6.5 mg/kg/day (1261 times the human AUC at the recommended human ophthalmic dose).

Pregnant cynomolgus monkeys were administered moxifloxacin at doses of 10, 30, or 100 mg/kg/day by intragastric intubation between Gestation Days 20 and 50, targeting the period of organogenesis. At the maternal toxic doses of ≥ 30 mg/kg/day, increased abortion, vomiting and diarrhea were observed. Smaller fetuses/reduced fetal body weights were observed at 100 mg/kg/day (14688 times the human AUC at the recommended human ophthalmic dose). The NOAEL for fetal toxicity was 10 mg/kg/day (894 times the human AUC at the recommended human ophthalmic dose).

In a pre- and postnatal study, rats were administered moxifloxacin by oral gavage at doses of 20, 100, and 500 mg/kg/day from Gestation Day 6 until the end of lactation. Maternal death occurred during gestation at 500 mg/kg/day. Slight increases in the duration of pregnancy, reduced pup birth weight, and decreased prenatal and neonatal survival were observed at 500 mg/kg/day (estimated 1420 times the human AUC at the recommended human ophthalmic dose). The NOAEL for pre- and postnatal development was 100 mg/kg/day (estimated 152 times the human AUC at the recommended human ophthalmic dose).

8.2 Lactation

Risk Summary

There are no data regarding the presence of moxifloxacin ophthalmic solution in human milk, the effects on the breastfed infants, or the effects on milk production/excretion to inform risk of moxifloxacin ophthalmic solution to an infant during lactation. A study in lactating rats has shown transfer of moxifloxacin into milk following oral administration. Systemic levels of moxifloxacin following topical ocular administration are low [see Clinical Pharmacology (12.3)], and it is not known whether measurable levels of moxifloxacin would be present in maternal milk following topical ocular administration. The developmental and health benefits of breastfeeding should be considered along with the mother's clinical need for moxifloxacin ophthalmic solution and any potential adverse effects on the breastfed child from moxifloxacin ophthalmic solution.

8.4 Pediatric Use

The safety and effectiveness of moxifloxacin ophthalmic solution in infants below 4 months of age have not been established.

There is no evidence that the ophthalmic administration of moxifloxacin has any effect on weight bearing joints, even though oral administration of some quinolones has been shown to cause arthropathy in immature animals.

8.5 Geriatric Use

No overall differences in safety and effectiveness have been observed between elderly and younger patients.

11 DESCRIPTION

Moxifloxacin ophthalmic solution USP is a sterile solution for topical ophthalmic use.

Moxifloxacin hydrochloride is an 8-methoxy fluoroquinolone anti-infective, with a diazabicyclononyl ring at the C7 position.

Chemical Name: 1-Cyclopropyl-6-fluoro-1,4-dihydro-8- methoxy-7- [(4aS,7aS)-octahydro- 6H- pyrrolol [3,4-b] pyridin-6-yl]-4-oxo-3-quinolinecarboxylic acid, monohydrochloride.

Each mL of moxifloxacin ophthalmic solution USP, 0.5 % contains 5.45 mg moxifloxacin hydrochloride USP, equivalent to 5 mg moxifloxacin base.

Inactives: boric acid, sodium chloride, sorbitol, tyloxapol, xanthan gum, hydrochloric acid and/or sodium hydroxide to adjust pH, and water for injection.

Moxifloxacin ophthalmic solution USP, 0.5% is a greenish-yellow, isotonic solution with an osmolality of 300 to 370 mOsm/kg and a pH of approximately 7.4. Moxifloxacin hydrochloride is a slightly yellow to yellow crystalline powder.

USP pH and Osmolality tests are pending.

12 CLINICAL PHARMACOLOGY

12.1 Mechanism of Action

Moxifloxacin is a member of the fluoroquinolone class of anti-infective drugs [see Microbiology (12.4)].

12.3 Pharmacokinetics

Moxifloxacin steady-state plasma pharmacokinetics were evaluated in healthy adult male and female subjects who were administered multiple, bilateral, topical ocular doses of moxifloxacin ophthalmic solution two times daily for four days with a final dose on Day 5. The average steady-state AUC0 to 12 was 8.17 ± 5.31 ng*h/mL. Moxifloxacin Cmax following twice-daily bilateral ophthalmic administration of moxifloxacin 0.5% for 5 days is approximately 0.02% of that achieved with the oral formulation of moxifloxacin hydrochloride (Cmax following oral dosing of 400 mg AVELOX®, 4.5 ± 0.5 mcg/mL).

12.4 Microbiology

The antibacterial action of moxifloxacin results from inhibition of the topoisomerase II (DNA gyrase) and topoisomerase IV. DNA gyrase is an essential enzyme that is involved in the replication, transcription and repair of bacterial DNA. Topoisomerase IV is an enzyme known to play a key role in the partitioning of the chromosomal DNA during bacterial cell division.

The mechanism of action for quinolones, including moxifloxacin, is different from that of macrolides, aminoglycosides, or tetracyclines. Therefore, moxifloxacin may be active against pathogens that are resistant to these antibiotics and these antibiotics may be active against pathogens that are resistant to moxifloxacin. There is no cross-resistance between moxifloxacin and the aforementioned classes of antibiotics. Cross-resistance has been observed between systemic moxifloxacin and some other quinolones.

In vitro resistance to moxifloxacin develops via multiple-step mutations. Resistance to moxifloxacin occurs in vitro at a general frequency of between 1.8 x 10^-9 to <1x10^-11 for Gram-positive bacteria.

Moxifloxacin has been shown to be active against most strains of the following microorganisms, both in vitro and in clinical infections as described in the Indications and Usage section:

Aerococcus viridans*

Corynebacterium macginleyi*

Enterococcus faecalis*

Micrococcus luteus*

Staphylococcus arlettae*

Staphylococcus aureus

Staphylococcus capitis

Staphylococcus epidermidis

Staphylococcus haemolyticus

Staphylococcus hominis

Staphylococcus saprophyticus*

Staphylococcus warneri*

Streptococcus mitis*

Streptococcus pneumoniae

Streptococcus parasanguinis*

Escherichia coli*

Haemophilus influenza

Klebsiella pneumoniae*

Propionibacterium acnes

Chlamydia trachomatis*

*Efficacy for this organism was studied in fewer than 10 infections.

The following in vitro data are available, but their clinical significance in ophthalmic infections is unknown. The safety and effectiveness of moxifloxacin ophthalmic solution in treating ophthalmic infections due to these organisms have not been established in adequate and well-controlled trials.

Moxifloxacin has been shown to be active in vitro against most strains of the microorganisms listed below. These organisms are considered susceptible when evaluated using systemic breakpoints; however, a correlation between the in vitro systemic breakpoint and ophthalmologic efficacy has not been established. The list of organisms is provided as guidance only in assessing the potential treatment of conjunctival infections. Moxifloxacin exhibits in vitro minimal inhibitory concentrations (MICs) of 2 mcg/mL or less (systemic susceptible breakpoint) against most (≥90%) strains of the following ocular pathogens.

Aerobic Gram-Positive Microorganisms

Staphylococcus caprae

Staphylococcus cohnii

Staphylococcus lugdunensis

Staphylococcus pasteuri

Streptococcus agalactiae

Streptococcus milleri group

Streptococcus oralis

Streptococcus pyogenes

Streptococcus salivarius

Streptococcus sanguis

Aerobic Gram-Negative Microorganisms

Acinetobacter baumannii

Acinetobacter calcoaceticus

Acinetobacter junii

Enterobacter aerogenes

Enterobacter cloacae

Haemophilus parainfluenzae

Klebsiella oxytoca

Moraxella catarrhalis

Moraxella osloensis

Morganella morganii

Neisseria gonorrhoeae

Neisseria meningitides

Pantoea agglomerans

Proteus vulgaris

Pseudomonas stutzeri

Serratia liquefaciens

Serratia marcescens

Stenotrophomonas maltophilia

Anaerobic Microorganisms

Clostridium perfringens

Peptostreptococcus anaerobius

Peptostreptococcus magnus

Peptostreptococcus micros

Peptostreptococcus prevotii

Other Microorganisms

Mycobacterium tuberculosis

Mycobacterium avium

Mycobacterium kansasii

Mycobacterium marinum

13 NONCLINICAL TOXICOLOGY

13.1 Carcinogenesis, Mutagenesis, Impairment of Fertility

Carcinogenesis

Long-term studies in animals to determine the carcinogenic potential of moxifloxacin have not been performed. However, in an accelerated study with initiators and promoters, moxifloxacin was not carcinogenic in rats following up to 38 weeks of oral dosing at 500 mg/kg/day (4741 times the recommended daily human ophthalmic dose for a 60 kg person, based on body surface area).

Mutagenesis

Moxifloxacin was not mutagenic in four bacterial strains used in the Ames Salmonella reversion assay. As with other quinolones, the positive response observed with moxifloxacin in strain TA 102 using the same assay may be due to the inhibition of DNA gyrase. Moxifloxacin was not mutagenic in the CHO/HGPRT mammalian cell gene mutation assay. An equivocal result was obtained in the same assay when v79 cells were used. Moxifloxacin was clastogenic in the v79 chromosome aberration assay, but it did not induce unscheduled DNA synthesis in cultured rat hepatocytes. There was no evidence of genotoxicity in vivo in a micronucleus test or a dominant lethal test in mice.

Impairment of Fertility

Moxifloxacin had no effect on fertility in male and female rats at oral doses as high as 500 mg/kg/day, approximately 4741 times the highest recommended daily human ophthalmic dose. At 500 mg/kg/day orally there were slight effects on sperm morphology (head-tail separation) in male rats and on the estrous cycle in female rats.

14 CLINICAL STUDIES

In one randomized, double-masked, multicenter, vehicle-controlled clinical trial in which patients with bacterial conjunctivitis were dosed with moxifloxacin ophthalmic solution 2 times a day, moxifloxacin ophthalmic solution was superior to its vehicle for both clinical and microbiological outcomes. Clinical cure achieved on Day 4 was 63% (265/424) in moxifloxacin ophthalmic solution treated patients, versus 51% (214/423) in vehicle-treated patients. Microbiologic success (eradication of baseline pathogens) was achieved on Day 4 in 75% (316/424) of moxifloxacin ophthalmic solution-treated patients versus 56% (237/423) of vehicle treated patients. Microbiologic eradication does not always correlate with clinical outcome in anti-infective trials.

16 HOW SUPPLIED/STORAGE AND HANDLING

Moxifloxacin ophthalmic solution USP, 0.5% is supplied as a sterile ophthalmic solution in a sterile 5 mL natural low density polyethylene bottle fitted with a natural low density polyethylene nozzle and sealed with a tan coloured high density polyethylene cap as follows:

3 mL in a 5 mL bottle (NDC 68180-421-01)

Storage: Store at 2°C to 25°C (36°F to 77°F).

17 PATIENT COUNSELING INFORMATION

Avoid Contamination of the Product

Advise patients not to touch the dropper tip to any surface to avoid contaminating the contents.

Avoid Contact Lens Wear

Advise patients not to wear contact lenses if they have signs and symptoms of bacterial conjunctivitis.

Hypersensitivity Reactions

Systemically administered quinolones, including moxifloxacin, have been associated with hypersensitivity reactions, even following a single dose. Advise patients to discontinue use immediately and contact their physician at the first sign of a rash or allergic reaction [see Warnings and Precautions (5.2)].

AVELOX® is the registered trademark of the Bayer AG and is not the trademark of Lupin Limited.

LUPIN and the are registered trademarks of Lupin Pharmaceuticals, Inc.

Manufactured for:

Lupin Pharmaceuticals, Inc.

Naples, FL 34108

United States.

Manufactured by:

Lupin Limited

Pithampur (M. P.) - 454 775

India.

Revised: November 2024 ID: 277377

PACKAGE LABEL.PRINCIPAL DISPLAY PANEL

Moxifloxacin Ophthalmic Solution USP, 0.5%

NDC 68180-421-01